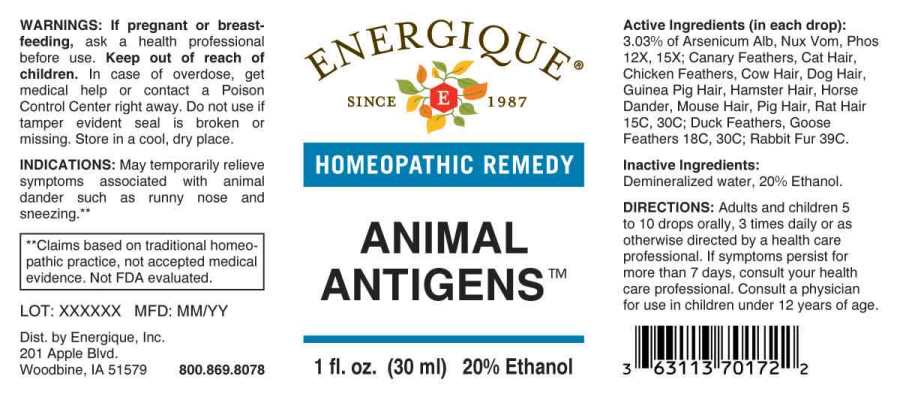 DRUG LABEL: Animal Antigens
NDC: 44911-0557 | Form: LIQUID
Manufacturer: Energique, Inc.
Category: homeopathic | Type: HUMAN OTC DRUG LABEL
Date: 20240716

ACTIVE INGREDIENTS: ARSENIC TRIOXIDE 12 [hp_X]/1 mL; STRYCHNOS NUX-VOMICA SEED 12 [hp_X]/1 mL; PHOSPHORUS 12 [hp_X]/1 mL; SERINUS CANARIA FEATHER 15 [hp_C]/1 mL; FELIS CATUS HAIR 15 [hp_C]/1 mL; GALLUS GALLUS FEATHER 15 [hp_C]/1 mL; BOS TAURUS HAIR 15 [hp_C]/1 mL; CANIS LUPUS FAMILIARIS HAIR 15 [hp_C]/1 mL; CAVIA PORCELLUS HAIR 15 [hp_C]/1 mL; MESOCRICETUS AURATUS SKIN 15 [hp_C]/1 mL; EQUUS CABALLUS DANDER 15 [hp_C]/1 mL; MUS MUSCULUS HAIR 15 [hp_C]/1 mL; SUS SCROFA HAIR 15 [hp_C]/1 mL; RATTUS NORVEGICUS HAIR 15 [hp_C]/1 mL; ANAS PLATYRHYNCHOS FEATHER 18 [hp_C]/1 mL; ANSER ANSER FEATHER 18 [hp_C]/1 mL; ORYCTOLAGUS CUNICULUS HAIR 39 [hp_C]/1 mL
INACTIVE INGREDIENTS: WATER; ALCOHOL

DRUG FACTS:

ACTIVE INGREDIENTS:

(in each drop): 3.03% of Arsenicum Album 12X, 15X, Nux Vomica 12X, 15X, Phosphorus 12X, 15X, Canary Feathers 15C, 30C, Cat Hair Mix 15C, 30C, Chicken Feathers 15C, 30C, Cow Hair 15C, 30C, Dog Hair Mix 15C, 30C, Guinea Pig Hair 15C, 30C, Hamster Hair 15C, 30C, Horse Dander 15C, 30C, Mouse Hair 15C, 30C, Pig Hair 15C, 30C, Rat Hair 15C, 30C; Duck Feathers 18C, 30C, Goose Feathers 18C, 30C, Rabbit Fur 39C.

INDICATIONS:

May temporarily relieve symptoms associated with animal dander such as runny nose and sneezing.**

**Claims based on traditional homeopathic practice, not accepted medical evidence. Not FDA evaluated.

WARNINGS:

If pregnant or breast-feeding, ask a health professional before use.

Keep out of reach of children. In case of overdose, get medical help or contact a Poison Control Center right away.

Do not use if tamper evident seal is broken or missing.

Store in a cool, dry place.

KEEP OUT OF REACH OF CHILDREN:

In case of overdose, get medical help or contact a Poison Control Center right away.

DIRECTIONS:

Adults and children 5 to 10 drops orally, 3 times daily or as otherwise directed by a health care professional. If symptoms persist for more than 7 days, consult your health care professional. Consult a physician for use in children under 12 years of age.

INDICATIONS:

May temporarily relieve symptoms associated with animal dander such as runny nose and sneezing.**

**Claims based on traditional homeopathic practice, not accepted medical evidence. Not FDA evaluated.

INACTIVE INGREDIENTS:

Demineralized water, 20% Ethanol.

QUESTIONS:

Dist. by Energique, Inc.

201 Apple Blvd.

Woodbine, IA 51579 800.869.8078

PACKAGE LABEL DISPLAY:

ENERGIQUE

SINCE 1987

HOMEOPATHIC REMEDY

ANIMAL ANTIGENS

1 fl. oz. (30 ml)